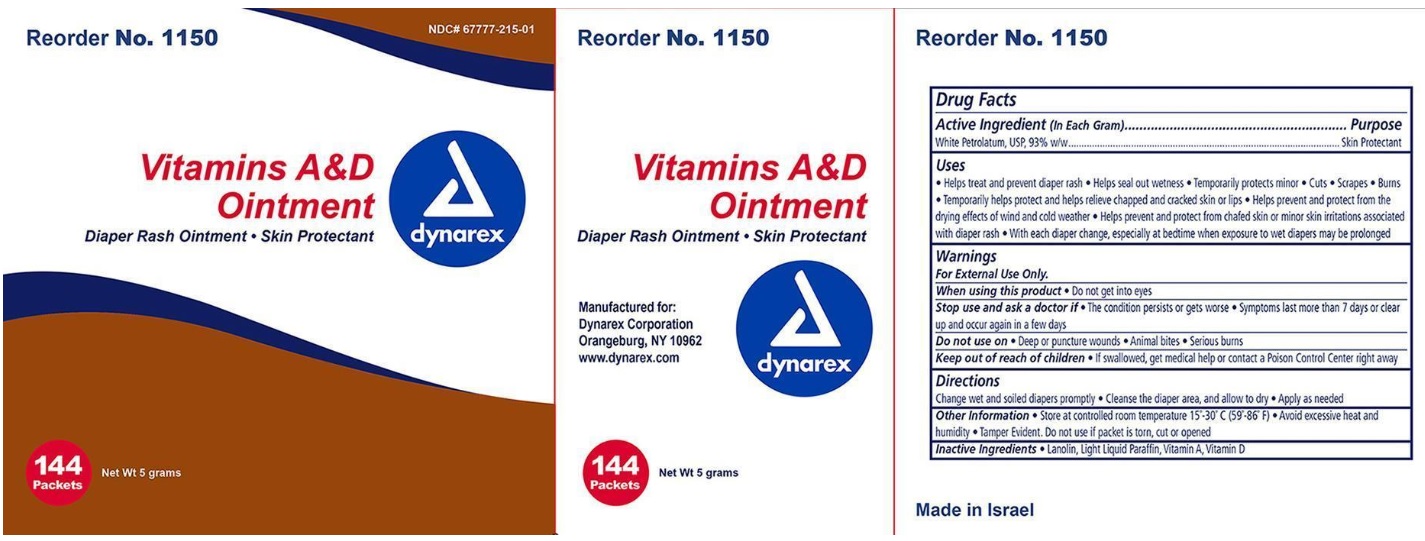 DRUG LABEL: Vitamin A D
NDC: 67777-215 | Form: OINTMENT
Manufacturer: Dynarex Corporation
Category: otc | Type: HUMAN OTC DRUG LABEL
Date: 20221212

ACTIVE INGREDIENTS: PETROLATUM 0.93 g/1 g
INACTIVE INGREDIENTS: VITAMIN A PALMITATE; CHOLECALCIFEROL; LANOLIN; LIGHT MINERAL OIL

Vitamin A D

Active Ingredient

White Petrolatum USP 93% w/w

Purpose

Skin Protectant

Uses

- Helps treat and prevent diaper rash
- Helps seal out wetness
- Temporarily protects minor * cuts * scrapes * burns
- Temporarily helps protect and help relieve chapped and cracked skin and lips
- Helps prevent and protect from the drying effects of wind and cold weather
- Helps prevent and protect chafed skin or minor skin irritations associated with diaper rash
- With each diaper change, especially at bedtime when exposure to wet diapers may be prolonged

Warnings:

For External Use Only

When using this product

Do not get into eyes

Stop use and ask a doctor if:

- The condition persists or gets worse
- Symptoms last more than 7 days or clear up and occur again in a few days

Do not use on:

- Deep or puncture wounds
- Animal bites
- Serious burns

Keep out of reach of children

If swallowed, get medical help or contact a Poison Control Center right away.

Directions:

- Change wet and soiled diapers promptly
- Cleanse the diaper area and allow to dry
- Apply as needed

Other information:

- Store at room temperature 15°-30°C (59° - 86°F)
- Avoid excessive heat and humidity
- Tamper Evident. Do not use if packet is torn, cut or opened

Inactive Ingredients

Lanolin, Light Liquid Paraffin, Vitamin A, Vitamin D

Principal Display Panel

NDC 67777-215-01

Vitamins A & D Ointment

Diaper Rash Ointment

Skin Protectant

144 Packets

Net Wt 5 grams